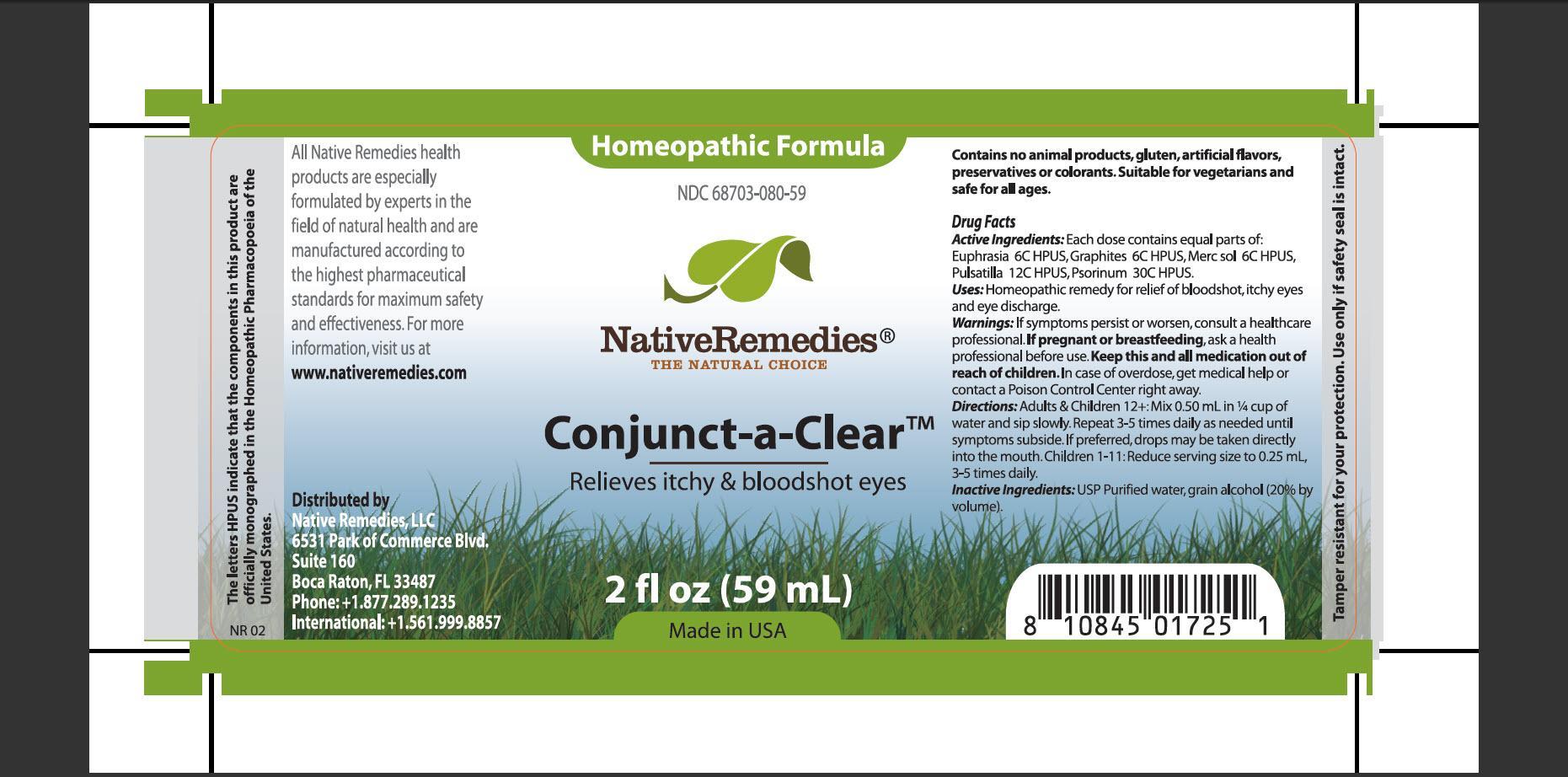 DRUG LABEL: Conjunct-a-Clear
NDC: 68703-080 | Form: TINCTURE
Manufacturer: Native Remedies, LLC
Category: homeopathic | Type: HUMAN OTC DRUG LABEL
Date: 20130424

ACTIVE INGREDIENTS: EUPHRASIA STRICTA 6 [hp_C]/1 mL; GRAPHITE 6 [hp_C]/1 mL; MERCURIUS SOLUBILIS 6 [hp_C]/1 mL; PULSATILLA VULGARIS 12 [hp_C]/1 mL; SCABIES LESION LYSATE (HUMAN) 30 [hp_C]/1 mL
INACTIVE INGREDIENTS: WATER; ALCOHOL

Conjunct-a-Clear

PURPOSE

Relieves itchy and bloodshot eyes

ACTIVE INGREDIENT

Active Ingredients: Each dose contains equal parts of: Euphrasia 6C HPUS, Graphites 6C HPUS, Merc sol 6C HPUS, Pulsatilla 12C HPUS, Psorinum 30C HPUS

INDICATIONS AND USAGE

Uses: Homeopathic remedy for relief of bloodshot, itchy eyes and eye discharge

WARNINGS

Warnings: If symptoms persist or worsen, consult a healthcare professional

PREGNANCY OR BREAST FEEDING

If pregnant or breastfeeding, ask a health professional before use

KEEP OUT OF REACH OF CHILDREN

Keep this and all medication out of reach of children

OVERDOSAGE

In case of overdose, get medical help or contact a Poison Control Center right away

DOSAGE AND ADMINISTRATION

Directions:Adults and Children 12+: Mix 0.50 mL in 1/4 cup of water and sip slowly. Repeat 3-5 times daily as needed until symptoms subside. If preferred, drops may be taken directly into the mouth. Children 1-11: Reduce serving size to 0.25 mL, 3-5 times daily

INACTIVE INGREDIENT

Inactive Ingredients: USP Purified water, grain alcohol (20% by volume)

PATIENT COUNSELING INFORMATION

The letters HPUS indicate that the component in this products are officially monographed in the Homeopathic Pharmacopoeia of the United States

All Native Remedies products are especially formulated by experts in the field of natural health and are manufactured according to the highest pharmaceutical standards for maximum safety and effectiveness. For more information, visit us at www.nativeremedies.com

Distributed by
Native Remedies, LLC
6531 Park of Commerce Blvd.
Suite 160
Boca Raton, FL 33487
Phone: +1.877.289.1235
International:+1.561.999.8857

Contains no animal products, glutenm artificial flavors, preservatives or colorants. Suitable for vegetarians and safe for all ages

STORAGE AND HANDLING

Tamper resistant for your protection. Use only if safety seal in intact